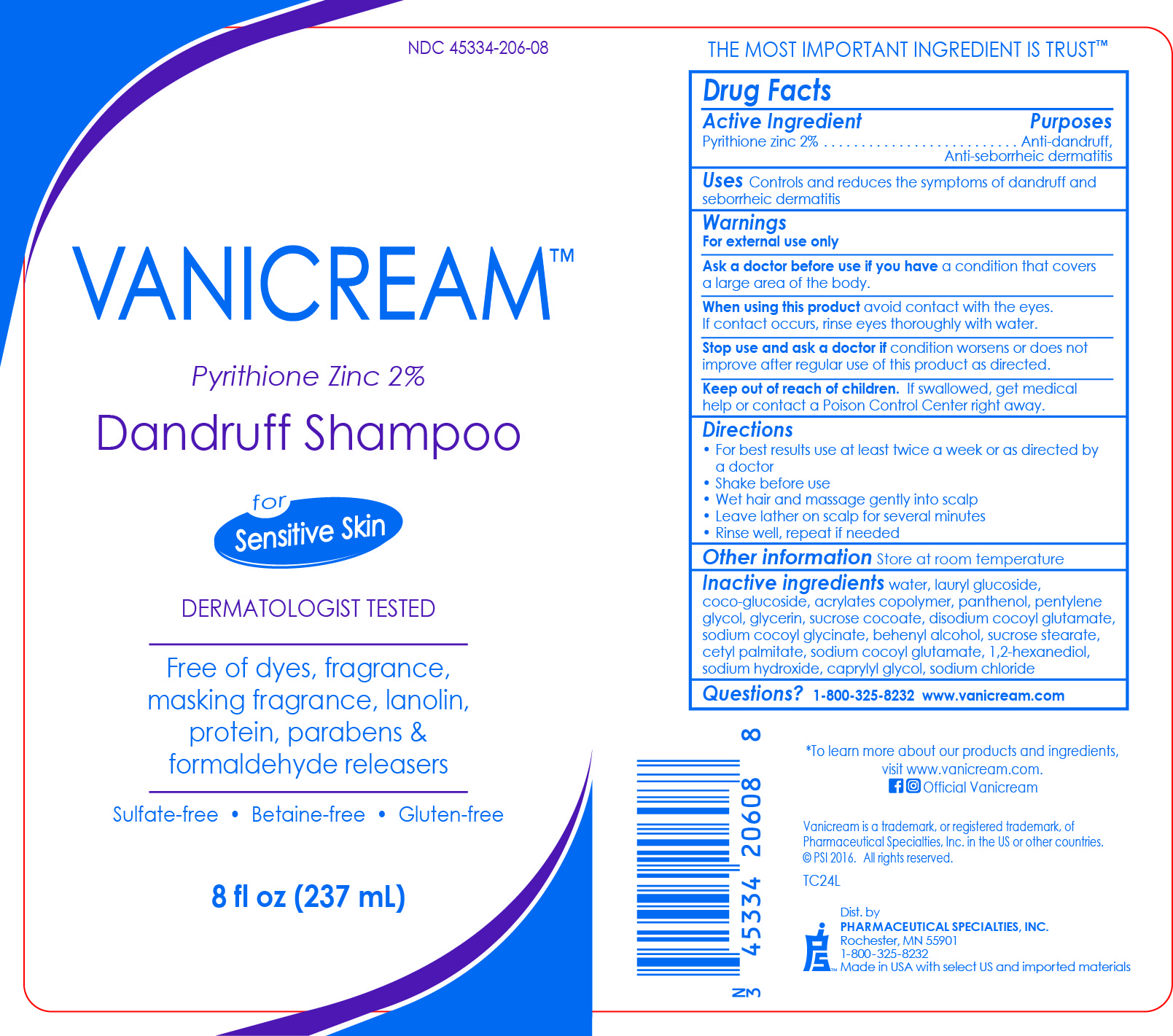 DRUG LABEL: Vanicream
NDC: 45334-206 | Form: SHAMPOO
Manufacturer: Pharmaceutical Specialties, Inc.
Category: otc | Type: HUMAN OTC DRUG LABEL
Date: 20241127

ACTIVE INGREDIENTS: PYRITHIONE ZINC 2 g/100 mL
INACTIVE INGREDIENTS: 1,2-HEXANEDIOL; METHACRYLIC ACID - ETHYL ACRYLATE COPOLYMER (4500 MPA.S); SUCROSE COCOATE; SUCROSE STEARATE; CAPRYLYL GLYCOL; COCO GLUCOSIDE; SODIUM COCOYL GLYCINATE; WATER; DOCOSANOL; PENTYLENE GLYCOL; GLYCERIN; DEXPANTHENOL; LAURYL GLUCOSIDE; DISODIUM COCOYL GLUTAMATE; CETYL PALMITATE; SODIUM COCOYL GLUTAMATE; SODIUM HYDROXIDE; SODIUM CHLORIDE

VANICREAM™ Dandruff Shampoo

Drug Facts

Active Ingredient

Pyrithione zinc 2%

Purposes

Anti-dandruff,

Anti-seborrheic dermatitis

Uses

Controls and reduces the symptoms of dandruff and seborrheic dermatitis

Warnings

For external use only

Ask a doctor before use if you have a condition that covers a large area of the body.

When using this product avoid contact with the eyes. If contact occurs, rinse eyes thoroughly with water.

Stop use and ask a doctor if condition worsens or does not improve after regular use of this product as directed.

Keep out of reach of children. If swallowed, get medical help or contact a Poison Control Center right away.

Directions

- For best results use at least twice a week or as directed by a doctor
- Shake before use
- Wet hair and massage gently into scalp
- Leave lather on scalp for several minutes
- Rinse well, repeat if needed

Other information

Store at room temperature

INACTIVE INGREDIENT

Inactive ingredientswater, lauryl glucoside, coco-glucoside, acrylates copolymer, panthenol, pentylene glycol, glycerin, sucrose cocoate, disodium cocoyl glutamate, sodium cocoyl glycinate, behenyl alcohol, sucrose stearate, cetyl palmitate, sodium cocoyl glutamate, 1,2-hexanediol, sodium hydroxide, caprylyl glycol, sodium chloride

Questions?

1-800-325-8232

www.vanicream.com

Dist. by

PHARMACEUTICAL SPECIALTIES, INC.

ROCHESTER, MN 55901

1-800-325-8232

Made in USA with select US and imported materials

PACKAGE LABEL

NDC 45334-206-08

VANICREAM™

Pyrithione Zinc 2%

Dandruff Shampoo

for Sensitive Skin

DERMATOLOGIST TESTED

Free of dyes, fragrance, masking fragrance, lanolin, protein, parabens, & formaldehyde releasers

Sulfate-free • Betaine-free • Gluten-free

8 fl oz (237 mL)